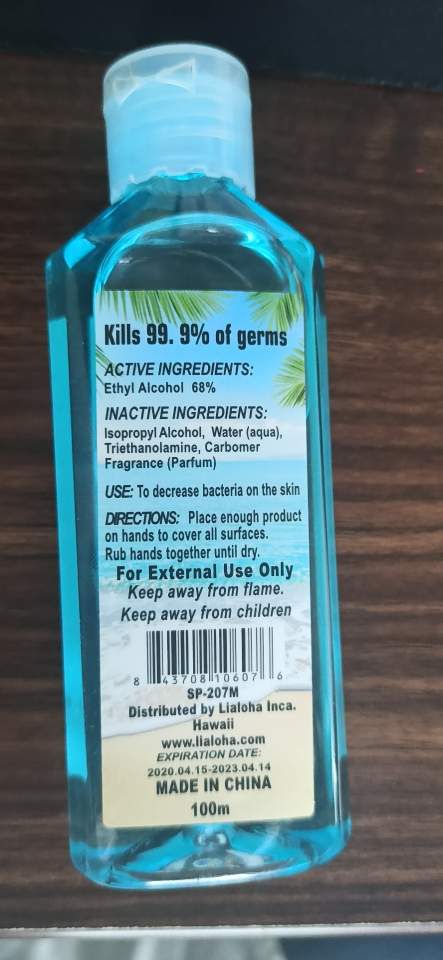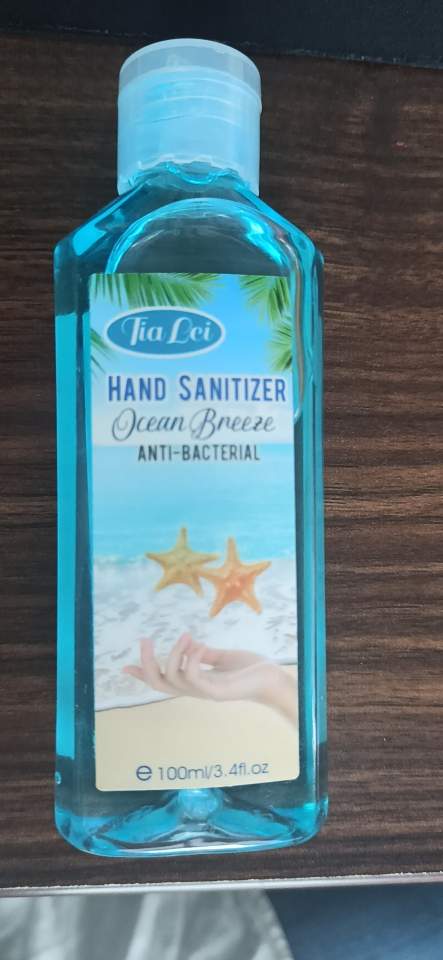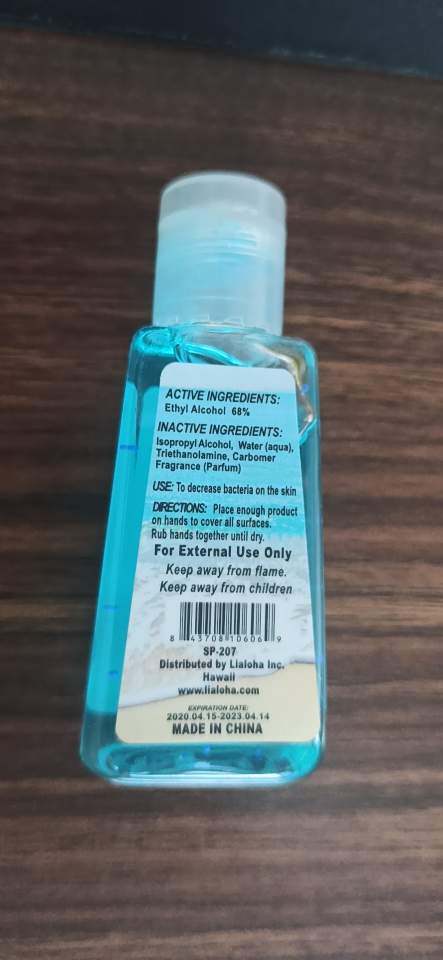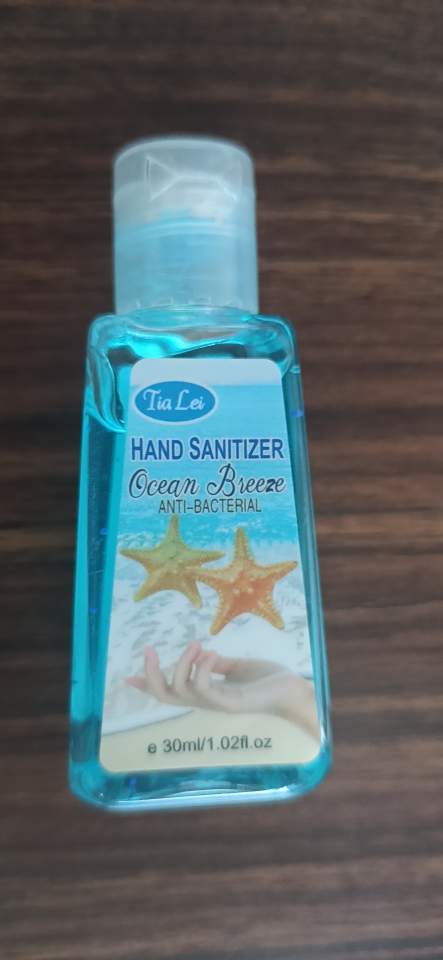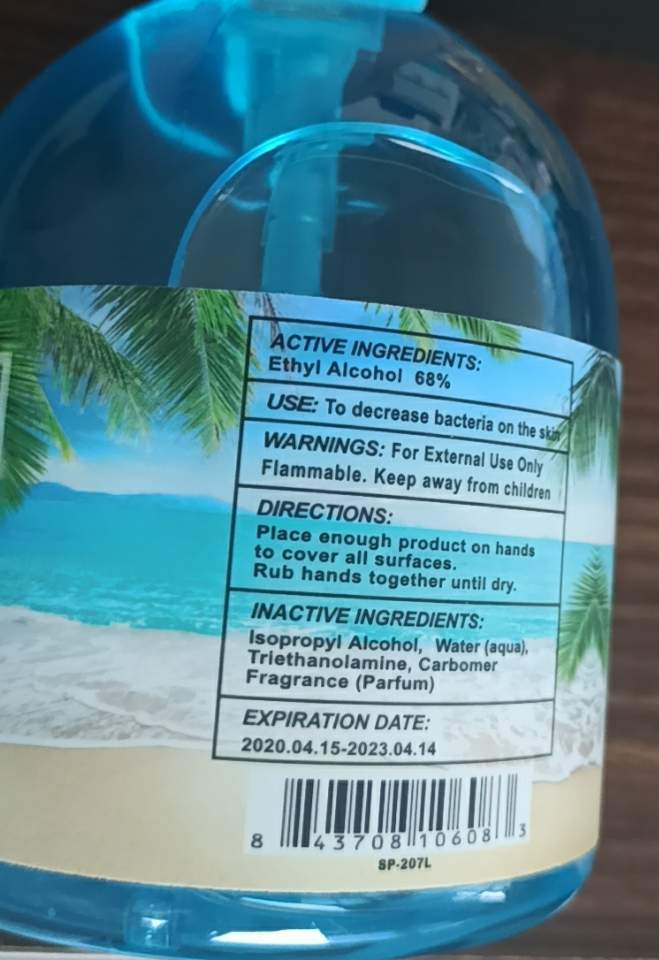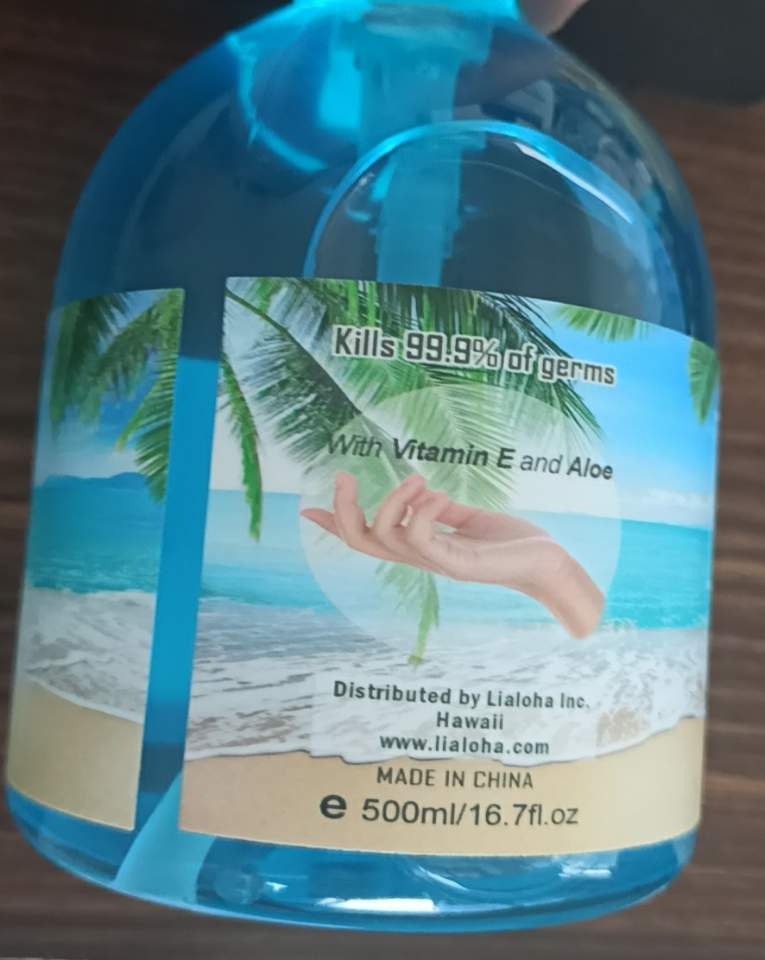 DRUG LABEL: Hand Sanitizer Ocean Breeze
NDC: 54225-005 | Form: GEL
Manufacturer: Yiwu Sloggi Cosmetics Co.,ltd
Category: otc | Type: HUMAN OTC DRUG LABEL
Date: 20211209

ACTIVE INGREDIENTS: ALCOHOL 68 mL/68 mL
INACTIVE INGREDIENTS: CARBOMER 940; ISOPROPYL ALCOHOL; WATER

Active Ingredient(s): Ethyl Alcohol 68%

Purpose: Antiseptic

DOSAGE AND ADMINISTRATION

Place enough product on hands to cover all surfaces.

WARNINGS

For external use only.

INACTIVE INGREDIENT

Isopropyl Alcohol

Water

Triethanolamine

Fragrance

INDICATIONS AND USAGE

Rub hands together until dry.

Keep away from children.

PACKAGE LABEL

30mL Ocean Breeze NDC 54225-005-01

100mL Ocean Breeze NDC 54225-005-02

500mL Ocean Breeze NDC 54225-005-03